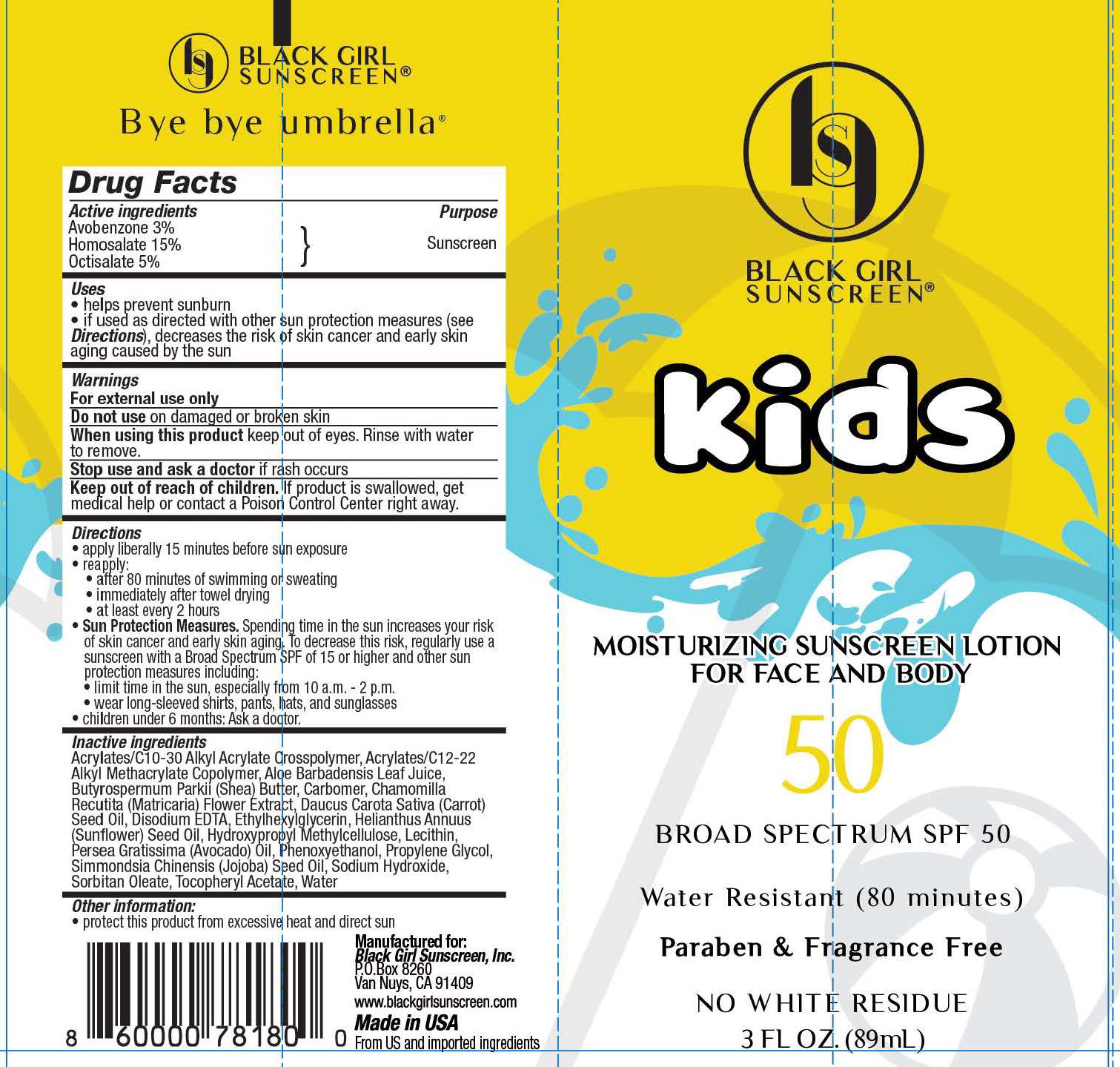 DRUG LABEL: Black Girl Sunscreen
NDC: 84204-0004 | Form: LOTION
Manufacturer: Black Girl Sunscreen, LLC
Category: otc | Type: HUMAN OTC DRUG LABEL
Date: 20250115

ACTIVE INGREDIENTS: AVOBENZONE 29.16 mg/1 mL; HOMOSALATE 145.8 mg/1 mL; OCTISALATE 48.6 mg/1 mL
INACTIVE INGREDIENTS: CARBOMER INTERPOLYMER TYPE A (ALLYL SUCROSE CROSSLINKED); ALOE VERA LEAF; EDETATE DISODIUM; LECITHIN, SOYBEAN; AVOCADO OIL; PHENOXYETHANOL; CARROT SEED OIL; ETHYLHEXYLGLYCERIN; WATER; PROPYLENE GLYCOL; SUNFLOWER SEED; HYPROMELLOSES; JOJOBA OIL; SORBITAN MONOOLEATE; .ALPHA.-TOCOPHEROL ACETATE; CARBOMER 980; SODIUM HYDROXIDE; BUTYL ACRYLATE/C16-C20 ALKYL METHACRYLATE/METHACRYLIC ACID/METHYL METHACRYLATE COPOLYMER; SHEA BUTTER; CHAMOMILE

Black Girl Sunscreen Kids Moisturizing Sunscreen Lotion for Face and Body 50 Broad Spectrum SPF 50

Active Ingredients

Avobenzone 3%

Homosalate 15%

Octisalate 5%

Purpose

Sunscreen

Uses

- helps prevent sunburn
- if used as directed with other sun protection measures (see Directions), decreses the risk of skin cancer and early skin aging caused by the sun

Warnings

For external use only

Do not useon damaged or broken skin

WHEN USING

When using this productkeep out of eyes. Rinse with water to remove.

Stop use and ask a doctorif rash occurs

Keep out of reach of children.If product is swallowed, get medical help or contact a Poison Control Center right away.

Directions

- apply liberally 15 minutes before sun exposure
- reapply
- after 80 minutes of swimming or sweating
- inmediately after towel drying
- at least every 2 hours
- Sun Protection Measures.Spending time in the sun increases your risk of skin cancer and early skin aging. To decrease this risk, regularly use a sunscreen with a Broad Spectrum SPF of 15 or higher and other sun protection measures, including:
- limit time in the sun, specially from 10 a.m. - 2 p.m.
- wear long-sleeve shirts, pants, hats & sunglasses.
- children under 6 months: Ask a doctor.

Inactive ingredients

Acrylates/C10-30 Alkyl Acrylate Crosspolymer, Acrylates/C12-22 Alkyl Methacrylate Copolymer, Aloe Barbadensis Leaf Juice, Butyrospermum Parkii (Shea) Butter, Carbomer, Chamomilla Recutita (Matricaria) Flower Extract, Daucus Carota Sativa (Carrot) Seed Oil, Disodium EDTA, Ethylhexylglycerin, Helianthus Annuus (Sunflower) Seed Oil, Hydroxypropyl Methylcellulose, Lecithin, Persea Gratissima (Avocado) Oil, Phenoxyethanol, Propylene Glycol, Simmondsia Chinensis (Jojoba) Seed Oil, Sodium Hydroxide, Sorbitan Oleate, Tocopheryl Acetate, Water

Other Information

- protect this product from excessive heat and direct sun